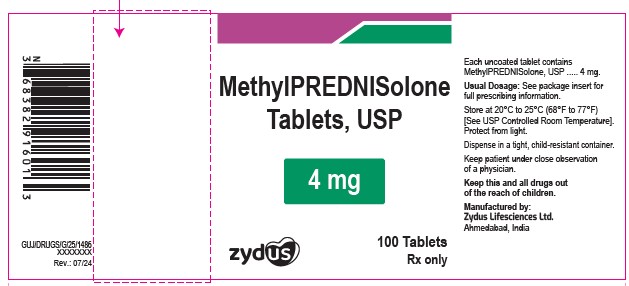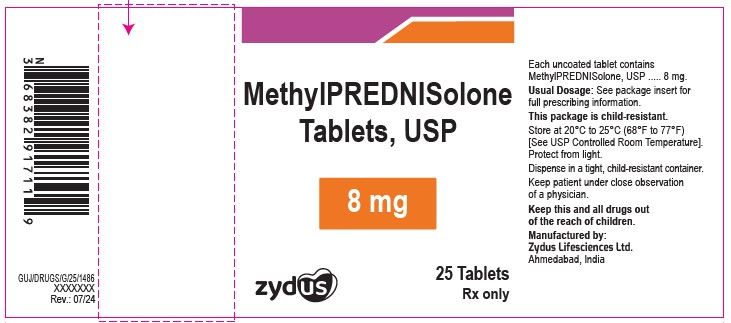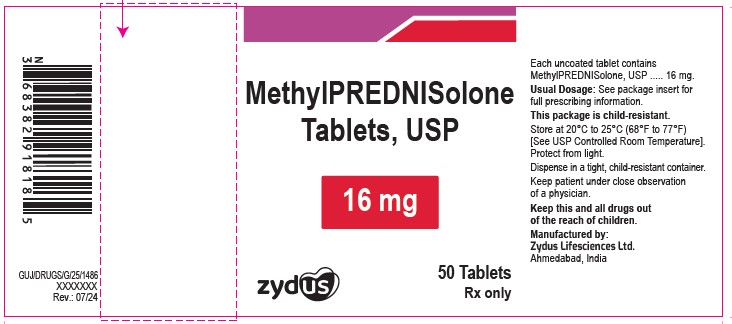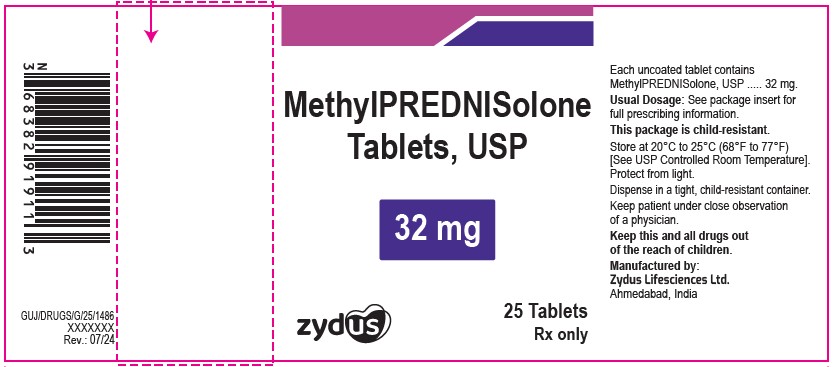 DRUG LABEL: methylprednisolone
NDC: 70771-1348 | Form: TABLET
Manufacturer: Zydus Lifesciences Limited
Category: prescription | Type: HUMAN PRESCRIPTION DRUG LABEL
Date: 20241205

ACTIVE INGREDIENTS: METHYLPREDNISOLONE 4 mg/1 1
INACTIVE INGREDIENTS: CELLULOSE, MICROCRYSTALLINE; LACTOSE MONOHYDRATE; MAGNESIUM STEARATE; SODIUM STARCH GLYCOLATE TYPE A POTATO; STARCH, CORN

Methylprednisolone Tablets, USP

PACKAGE LABEL.PRINCIPAL DISPLAY PANEL

NDC 70771-1348-1 in bottle of 100 tablets

Methylprednisolone tablets, USP

Rx only

100 tablets

NDC 70771-1349-8 in bottle of 25 tablets

Methylprednisolone tablets, USP

Rx only

25 tablets

NDC 70771-1350-7 in bottle of 50 tablets

Methylprednisolone tablets, USP

Rx only

50 tablets

NDC 70771-1351-8 in bottle of 25 tablets

Methylprednisolone tablets, USP

Rx only

25 tablets